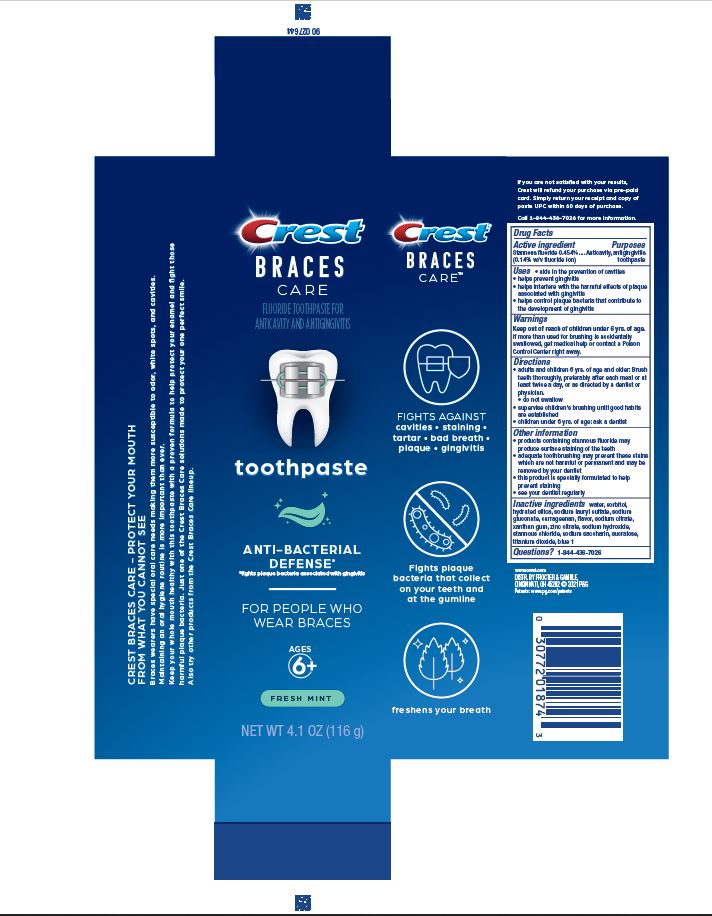 DRUG LABEL: Crest
NDC: 69423-879 | Form: PASTE, DENTIFRICE
Manufacturer: The Procter & Gamble Manufacturing Company
Category: otc | Type: HUMAN OTC DRUG LABEL
Date: 20251118

ACTIVE INGREDIENTS: STANNOUS FLUORIDE 1.4 mg/1 g
INACTIVE INGREDIENTS: SUCRALOSE; HYDRATED SILICA; SORBITOL; SODIUM CITRATE; ZINC CITRATE; WATER; SODIUM LAURYL SULFATE; SODIUM GLUCONATE; CARRAGEENAN; SACCHARIN SODIUM; XANTHAN GUM; TITANIUM DIOXIDE; SODIUM HYDROXIDE; FD&C BLUE NO. 1; STANNOUS CHLORIDE

Crest Braces Care Cavity Protection Toothpaste

Drug Facts

Active ingredient

Stannous fluoride 0.454% (0.14% w/v fluoride ion)

Purposes

Anticavity, antigingivitis toothpaste

Uses

- aids in the prevention of cavities
- helps prevent gingivitis
- helps interfere with the harmful effects of plaque associated with gingivitis
- helps control plaque bacteria that contribute to the development of gingivitis

Warnings

Keep out of reach of children under 6 yrs. of age. If more than used for brushing is accidentally swallowed, get medical help or contact a Poison Control Center right away.

Directions

- adults and children 6 yrs. of age & older: Brush teeth thoroughly, preferably after each meal or at least twice a day, or as directed by a dentist or physician.
- do not swallow
- supervise children's brushing until good habits are established
- children under 6 yrs.: ask a dentist

Other information

- products containing stannous fluoride may produce surface staining of the teeth
- adequate toothbrushing may prevent these stains which are not harmful or permanent and may be removed by your dentist
- this product is specially formulated to help prevent staining
- see your dentist regularly

Inactive ingredients

water, sorbitol, hydrated silica, sodium lauryl sulfate, sodium gluconate, carrageenan, flavor, sodium citrate, xanthan gum, zinc citrate, sodium hydroxide, stannous chloride, sodium saccharin, sucralose, titanium dioxide, blue 1

Questions?

1-844-436-7026

DISTR. BY PROCTER & GAMBLE,
CINCINNATI, OH 45202

Crest Braces Care Cavity Protection Toothpaste 99 g carton

Crest

BRACES

CARE

FLUORIDE TOOTHPASTE FOR

ANTICAVITY AND ANTIGINGIVITIS

toothpaste

ANTI-BACTERIAL

DEFENSE*

*fights plaque bacteria associated with gingivitis

FOR PEOPLE WHO

WEAR BRACES

AGES 6+

FRESH MINT

NET WT 4.1 OZ (116 g)